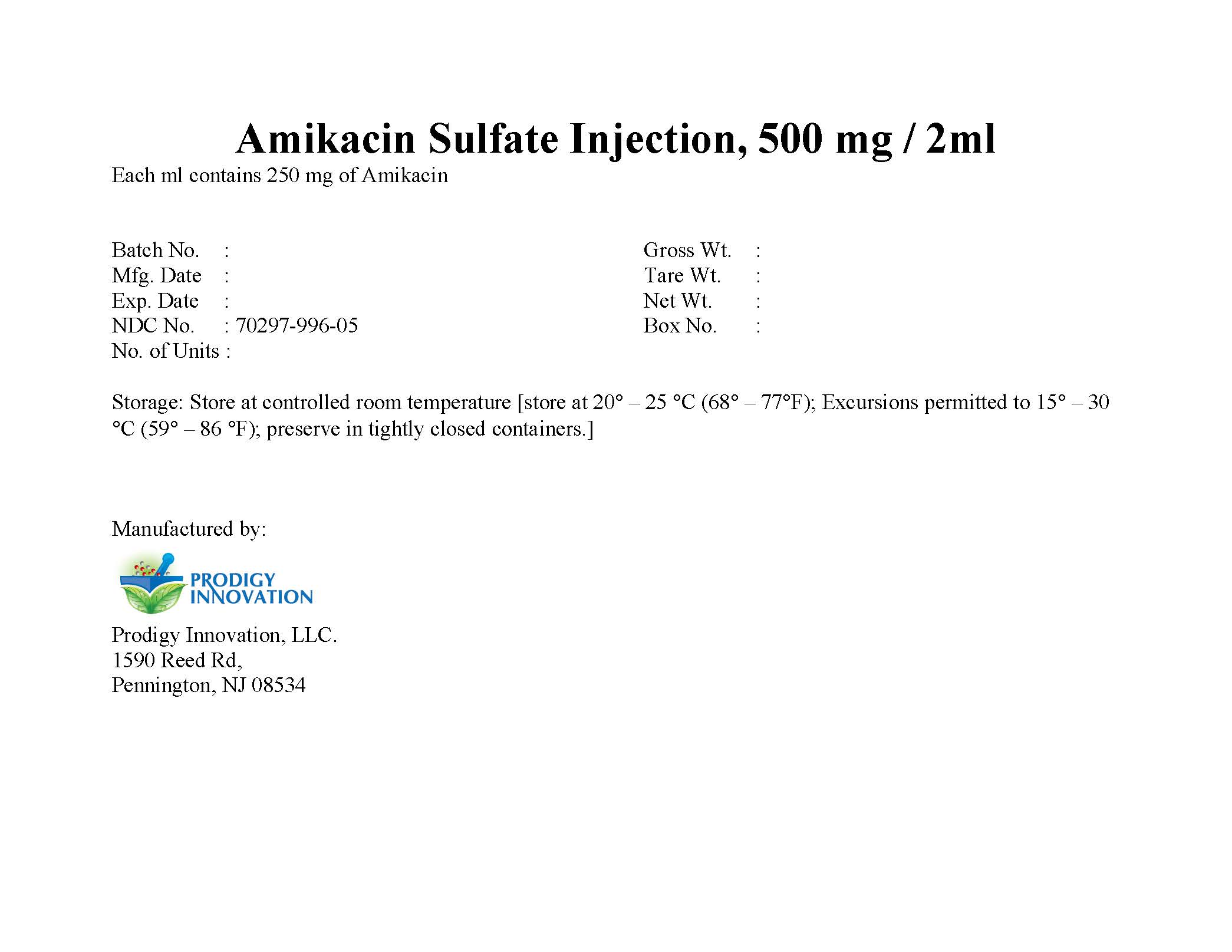 DRUG LABEL: Amikacin Sulfate Injection, 500 mg/2ml
NDC: 70297-996 | Form: INJECTION
Manufacturer: Prodigy Innovation, LLC.
Category: prescription | Type: HUMAN PRESCRIPTION DRUG LABEL
Date: 20190505

ACTIVE INGREDIENTS: AMIKACIN SULFATE 500 mg/1 1
INACTIVE INGREDIENTS: SULFURIC ACID; SODIUM METABISULFITE; SODIUM CITRATE

Amikacin Sulfate Injection, 500 mg / 2ml